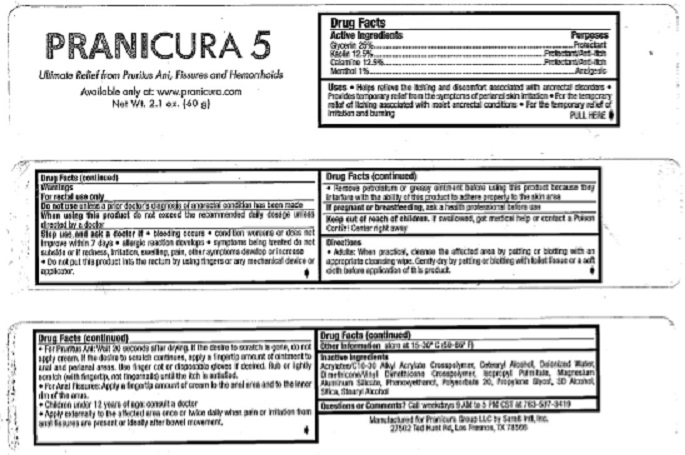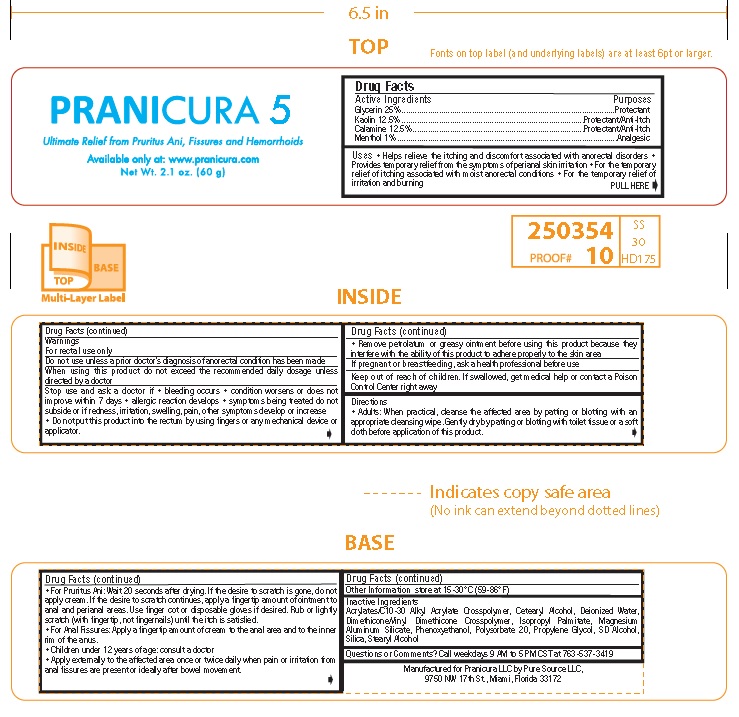 DRUG LABEL: Pranicura 5
NDC: 71831-004 | Form: CREAM
Manufacturer: Pranicura Products LLC
Category: otc | Type: HUMAN OTC DRUG LABEL
Date: 20251104

ACTIVE INGREDIENTS: GLYCERIN 25.0 g/100 g; KAOLIN 12.5 g/100 g; ZINC OXIDE 12.5 g/100 g; MENTHOL 1.0 g/100 g
INACTIVE INGREDIENTS: CARBOMER INTERPOLYMER TYPE A (ALLYL SUCROSE CROSSLINKED); CETOSTEARYL ALCOHOL; WATER; DIMETHICONE/VINYL DIMETHICONE CROSSPOLYMER (SOFT PARTICLE); ISOPROPYL PALMITATE; MAGNESIUM ALUMINUM SILICATE; PHENOXYETHANOL; POLYSORBATE 20; PROPYLENE GLYCOL; ALCOHOL; SILICON DIOXIDE; STEARYL ALCOHOL

PRANICURA 5

Drug Facts

Active Ingredients

Glycerin 25%
Kaolin 12.5%
Calamine 12.5%
Menthol 1%

Purposes

Glycerin ....................................................Protectant
Kaolin .........................................Protectant/Anti-Itch
Calamine ....................................Protectant/Anti-Itch
Menthol .....................................................Analgesic

INDICATIONS AND USAGE

Uses • Helps relieve the itching and discomfort associated with anorectal disorders •
Provides temporary relief from the symptoms of perianal skin irritation • For the temporary
relief of itching associated with moist anorectal conditions • For the temporary relief of
irritation and burning

Warnings
For rectal use only
Do not use unless a prior doctor’s diagnosis of anorectal condition has been made
When using this product do not exceed the recommended daily dosage unless
directed by a doctor
Stop use and ask a doctor if • bleeding occurs • condition worsens or does not
improve within 7 days • allergic reaction develops • symptoms being treated do not
subside or if redness, irritation, swelling, pain, other symptoms develop or increase
• Do not put this product into the rectum by using fingers or any mechanical device or
applicator.

• Remove petrolatum or greasy ointment before using this product because they
interfere with the ability of this product to adhere properly to the skin area
If pregnant or breastfeeding, ask a health professional before use

Keep out of reach of children. If swallowed, get medical help or contact a Poison
Control Center right away

Other Information store at 15-30º C (59-86º F)

Other Information store at 15-30º C (59-86º F)

Inactive Ingredients
Acrylates/C10-30 Alkyl Acrylate Crosspolymer, Cetearyl Alcohol, Deionized Water,
Dimethicone/Vinyl Dimethicone Crosspolymer, Isopropyl Palmitate, Magnesium
Aluminum Silicate, Phenoxyethanol, Polysorbate 20, Propylene Glycol, SD Alcohol,
Silica, Stearyl Alcohol

Questions or Comments? Call weekdays 9 AM to 5 PM CST at 763-537-3419

PACKAGE LABEL

PRANICURA 5

Ultimate Relief from Pruritus Ani, Fissures and Hemmorhoids

Available only at: www.pranicura.com

Net Wt. 2.1 oz. (60 g)

RES